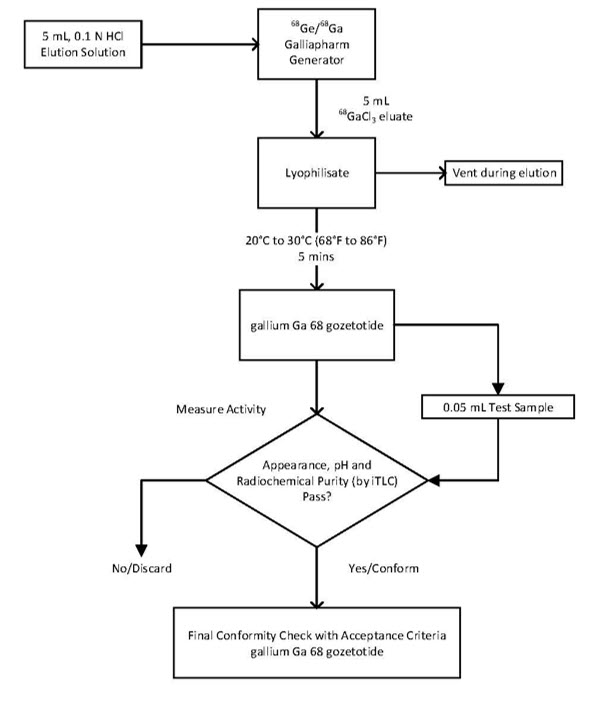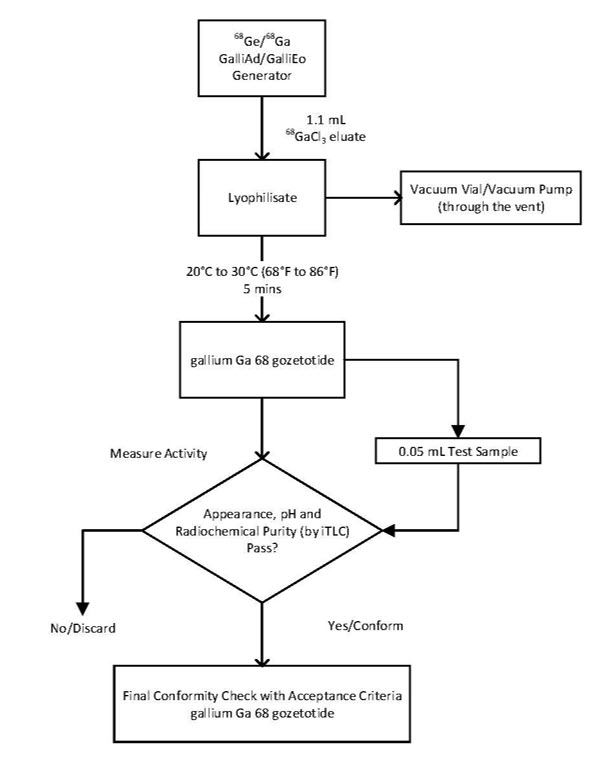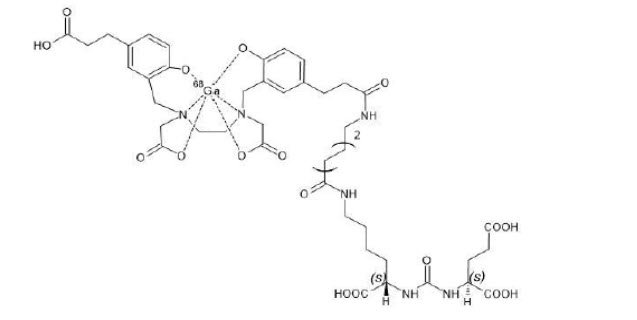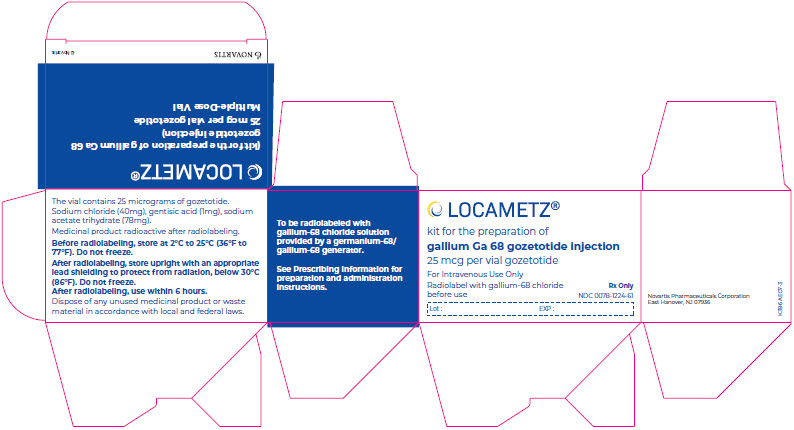 DRUG LABEL: LOCAMETZ
NDC: 0078-1224 | Form: INJECTION, POWDER, LYOPHILIZED, FOR SOLUTION
Manufacturer: Novartis Pharmaceuticals Corporation
Category: prescription | Type: HUMAN PRESCRIPTION DRUG LABEL
Date: 20260115

ACTIVE INGREDIENTS: GOZETOTIDE 25 ug/1 1
INACTIVE INGREDIENTS: SODIUM ACETATE; SODIUM CHLORIDE; GENTISIC ACID; WATER; NITROGEN

HIGHLIGHTS OF PRESCRIBING INFORMATION

These highlights do not include all the information needed to use LOCAMETZ safely and effectively. See full prescribing information for LOCAMETZ.
LOCAMETZ® (kit for the preparation of gallium Ga 68 gozetotide injection), for intravenous use
Initial U.S. Approval: 2020

RECENT MAJOR CHANGES

Indications and Usage (1) | 3/2025
Dosage and Administration, Image Interpretation (2.8) | 3/2025
Warnings and Precautions, Risk for Misinterpretation (5.1) | 3/2025

1 INDICATIONS AND USAGE

LOCAMETZ, after radiolabeling with gallium-68, is a radioactive diagnostic agent indicated for positron emission tomography (PET) of prostate-specific membrane antigen (PSMA)-positive lesions in men with prostate cancer:

- with suspected metastasis who are candidates for initial definitive therapy
- with suspected recurrence based on elevated serum prostate-specific antigen (PSA) level
- for selection of patients who are indicated for PSMA-directed therapy as described in the prescribing information of the therapeutic products. (1)

2 DOSAGE AND ADMINISTRATION

- Use appropriate radiation safety measures and aseptic precautions while handling and administering gallium Ga 68 gozetotide injection. (2.1)
- The recommended amount of radioactivity is 111 MBq to 259 MBq (3 mCi to 7 mCi). Administered as slow intravenous injection. (2.2)
- Advise patients to be well hydrated prior to the administration and to void immediately prior to and frequently after image acquisition. (2.3)
- A diuretic expected to act within the uptake time period may be administered at the time of radiotracer injection. (2.6)
- Acquire PET whole body images 50 minutes to 100 minutes after administration. (2.7)
- See the full prescribing information for detailed instructions on preparation, administration, imaging, and radiation dosimetry. (2)

3 DOSAGE FORMS AND STRENGTHS

- Kit for the preparation of gallium Ga 68 gozetotide injection supplied in a multiple-dose vial containing 25 mcg of gozetotide as a white lyophilized powder. After radiolabeling with gallium-68, the vial contains a sterile solution of gallium Ga 68 gozetotide at a strength up to 2,590 MBq (70 mCi) in up to 10 mL at calibration date and time. (3)

4 CONTRAINDICATIONS

None. (4)

5 WARNINGS AND PRECAUTIONS

- Risk for Misinterpretation: Gallium Ga 68 gozetotide uptake may occur in other tumor types and in non-malignant processes. Interpretation of LOCAMETZ PET imaging with histopathology and/or other diagnostic procedures is recommended. (5.1)
- Radiation Risk: Gallium Ga 68 gozetotide contributes to a patient’s overall long-term cumulative radiation exposure. Ensure safe handling and preparation procedures to protect patients and health care workers from unintentional radiation exposure. (5.2)

6 ADVERSE REACTIONS

The adverse reactions (incidence ≥ 0.5%) are fatigue, nausea, constipation, and vomiting. (6.1)

To report SUSPECTED ADVERSE REACTIONS, contact Novartis Pharmaceuticals Corporation at 1-888-669-6682 or FDA at 1-800-FDA-1088 or www.fda.gov/medwatch.

FULL PRESCRIBING INFORMATION

1 INDICATIONS AND USAGE

LOCAMETZ, after radiolabeling with gallium-68, is indicated for positron emission tomography (PET) of prostate-specific membrane antigen (PSMA)-positive lesions in men with prostate cancer:

- with suspected metastasis who are candidates for initial definitive therapy.
- with suspected recurrence based on elevated serum prostate-specific antigen (PSA) level.
- for selection of patients who are indicated for PSMA-directed therapy as described in the prescribing information of the therapeutic products.

2 DOSAGE AND ADMINISTRATION

2.1 Radiation Safety – Drug Handling

After reconstitution and radiolabeling of LOCAMETZ, the vial contains gallium Ga 68 gozetotide injection. Handle the gallium Ga 68 gozetotide injection with appropriate safety measures to minimize radiation exposure [see Warnings and Precautions (5.2)]. Use waterproof gloves, effective radiation shielding, and other appropriate safety measures when preparing and handling gallium Ga 68 gozetotide injection.

Radiopharmaceuticals should be used by or under the control of health care providers who are qualified by specific training and experience in the safe use and handling of radionuclides, and whose experience and training have been approved by the governmental agency authorized to license the use of radionuclides.

2.2 Recommended Dosage

In adults, the recommended amount of radioactivity to be administered for PET is 111 MBq to 259 MBq (3 mCi to 7 mCi) by slow intravenous injection.

2.3 Patient Preparation

Advise patients to be well hydrated prior to gallium Ga 68 gozetotide injection administration and to void immediately prior to and frequently during the first hours after image acquisition to reduce radiation exposure [see Warnings and Precautions (5.2)].

2.4 Drug Preparation

LOCAMETZ allows the direct preparation of gallium Ga 68 gozetotide injection with the eluate from one of the following generators (see below for specific instruction for use with each generator):

- Eckert & Ziegler GalliaPharm germanium-68/gallium-68 (^68Ge/^68Ga) generator
- IRE ELiT Galli Eo germanium-68/gallium-68 (^68Ge/^68Ga) generator

The instructions for use provided by the germanium-68/gallium-68 generator manufacturer should also be followed.

Prepare gallium Ga 68 gozetotide injection according to the following aseptic procedure:

a. Use suitable shielding to reduce radiation exposure.

b. Wear waterproof gloves.

c. Flip the cap off the LOCAMETZ vial and swab the septum with an appropriate antiseptic, then allow the septum to dry.

d. Pierce the LOCAMETZ vial septum with a sterile needle connected to a 0.2-micron sterile air venting filter to maintain atmospheric pressure within the vial during the reconstitution process.

e. Place the LOCAMETZ vial in a lead shield container.

f. Follow the generator specific procedures below. Schematic diagrams are provided in Figures 1 and 2.

Preparation with Eckert & Ziegler GalliaPharm Generator

1) Connect the male luer of the outlet line of the generator to a sterile elution needle (size 21G to 23G).

2) Connect the LOCAMETZ vial directly to the outlet line of the generator by pushing the elution needle through the rubber septum.

3) Elute directly from the generator into the LOCAMETZ vial.

4) Perform the elution manually or by means of a pump according to the generator instructions for use.

5) Reconstitute the lyophilized powder with 5 mL of eluate.

6) At the end of the elution, disconnect the LOCAMETZ vial from the generator by removing the elution needle and the vent needle with the 0.2-micron sterile air venting filter from the rubber septum. Then, invert LOCAMETZ vial once and place it upright.

7) Incubate the LOCAMETZ vial upright between 20°C to 30°C (68°F to 86°F) for at least 5 minutes without agitation or stirring.

8) After 5 minutes, assay the vial containing the gallium Ga 68 gozetotide injection for total radioactivity using a dose calibrator, calculate the radioactivity concentration and record the result.

9) After radiolabeling, gallium Ga 68 gozetotide injection may be diluted with Sterile Water for Injection, USP or 0.9% Sodium Chloride Injection, USP up to a final volume of 10 mL.

10) Perform quality controls according to the recommended methods in order to check compliance with the specifications [see Dosage and Administration (2.5)].

11) Store the LOCAMETZ vial containing the gallium Ga 68 gozetotide injection upright in a lead shield container below 30°C (86°F) until use.

12) After addition of gallium-68 chloride to the LOCAMETZ vial, use gallium Ga 68 gozetotide injection within 6 hours.

Preparation with IRE ELiT Galli Eo Generator

1) Connect the male luer of the outlet line of the generator to a sterile elution needle (size 21G to 23G).

2) Connect the LOCAMETZ vial directly to the outlet line of the generator by pushing the elution needle through the rubber septum.

3) Connect the LOCAMETZ vial through the vent needle with 0.2-micron sterile air venting filter to a vacuum vial (25 mL minimum volume) by means of a sterile needle (size 21G to 23G) or to a vacuum pump to start the elution.

4) Elute directly from the generator into the LOCAMETZ vial.

5) Reconstitute the lyophilized powder with 1.1 mL of eluate.

6) At the end of the elution, first withdraw the sterile needle from the vacuum vial or disconnect the vacuum pump in order to establish atmospheric pressure into the LOCAMETZ vial, then disconnect the vial from the generator by removing both the elution needle and the vent needle with the 0.2-micron sterile air venting filter needle from the rubber septum. Inversion of the LOCAMETZ vial is not needed.

7) Incubate the LOCAMETZ vial upright between 20°C to 30°C (68°F to 86°F) for at least 5 minutes without agitation or stirring.

8) After 5 minutes, assay the vial containing the gallium Ga 68 gozetotide injection for total radioactivity using a dose calibrator, calculate the radioactivity concentration and record the result.

9) After radiolabeling, gallium Ga 68 gozetotide injection may be diluted with Sterile Water for Injection, USP or 0.9% Sodium Chloride Injection, USP up to a final volume of 10 mL.

10) Perform quality controls according to the recommended methods in order to check compliance with the specifications [see Dosage and Administration (2.5)].

11) Store the LOCAMETZ vial containing the gallium Ga 68 gozetotide injection upright in a lead shield container below 30°C (86°F) until use.

12) After addition of gallium-68 chloride to the LOCAMETZ vial, use gallium Ga 68 gozetotide injection within 6 hours.

Figure 1. Preparation with Eckert & Ziegler GalliaPharm Generator

Figure 2. Preparation with IRE ELiT Galli Eo Generator

2.5 Specifications and Quality Control

Perform the quality controls in Table 1 behind a lead glass shield for radioprotection purposes.

Table 1. Specifications of Gallium Ga 68 Gozetotide Injection
Test | Acceptance criteria | Method
Appearance | Clear, colorless and free from particulate matter | Visual inspection
pH | 3.2 to 6.5 | pH-indicator strips
Radiochemical purity | gallium Ga 68 gozetotide ≥ 95% Non-complexed gallium-68 species ≤ 5% | Instant thin layer chromatography (ITLC, see details below)

Determine radiochemical purity of gallium Ga 68 gozetotide injection by performing instant thin layer chromatography (ITLC).

Perform ITLC using ITLC SG strips and using ammonium acetate 1M: Methanol (1:1 V/V) as mobile phase.

ITLC Method

a. Develop the ITLC SG strip for a distance of 6 cm from the point of application (i.e., to 7 cm from the bottom of the ITLC strip).

b. Scan the ITLC SG strip with a radiometric ITLC scanner.

c. Calculate radiochemical purity by integration of the peaks on the chromatogram. Do not use the reconstituted product if the percentage (%) of non-complexed gallium-68 species is higher than 5%.

The retention factor (Rf) specifications are as follows:

- Non-complexed gallium-68 species, Rf = 0 to 0.2;
- Gallium Ga 68 gozetotide, Rf = 0.8 to 1.

2.6 Administration

a. Use aseptic technique and radiation shielding when withdrawing and administering gallium Ga 68 gozetotide injection.

b. Calculate the necessary volume to administer based on calibration time and required dose.

c. Inspect the prepared gallium Ga 68 gozetotide injection for particulate matter and discoloration behind a lead glass shield for radioprotection purposes. Use only solutions that are clear, colorless and free from particulate matter.

d. Using a single-dose syringe fitted with a sterile needle (size 21G to 23G) and protective shielding, aseptically withdraw the prepared gallium Ga 68 gozetotide injection.

e. Verify the total radioactivity in the syringe with a dose calibrator immediately before and after gallium Ga 68 gozetotide injection administration to the patient. The dose calibrator must be calibrated with NIST traceable standards.

f. After injection of gallium Ga 68 gozetotide, administer an intravenous flush of sterile 0.9% Sodium Chloride Injection, USP to ensure full delivery of the dose.

g. Dispose of any unused gallium Ga 68 gozetotide injection in a safe manner in compliance with applicable regulations.

h. If clinically necessary, a diuretic expected to act within the uptake time period may be administered at the time of radiotracer injection to potentially decrease artifact from radiotracer accumulation in the urinary bladder and ureters.

2.7 Image Acquisition

Begin PET scanning 50 minutes to 100 minutes after the intravenous administration of gallium Ga 68 gozetotide injection. Patients should void immediately prior to image acquisition and image acquisition should begin at the mid-thighs and proceed cranially to the skull base or skull vertex. Adapt imaging technique according to the equipment used and patient characteristics in order to obtain the best image quality possible.

2.8 Image Interpretation

Gallium Ga 68 gozetotide binds to PSMA. Based on the intensity of the signals, PET images obtained using gallium Ga 68 gozetotide injection indicate the presence of PSMA in tissues.

Imaging Prior to Initial Definitive or Suspected Recurrence Therapy

Lesions should be considered suspicious if uptake is greater than physiologic uptake in that tissue or greater than adjacent background if no physiologic uptake is expected. Tumors that do not bear PSMA will not be visualized. Increased uptake in tumors is not specific for prostate cancer [see Warnings and Precautions (5.1)].

Imaging to Select Patients for PSMA-Directed Therapy

For instructions on patient selection, refer to the prescribing information of the PSMA-directed therapeutic product.

2.9 Radiation Dosimetry

Estimated radiation absorbed doses per injected activity for organs and tissues of 13 adult male patients with an early stage of disease following an intravenous bolus of gallium Ga 68 gozetotide injection are shown in Table 2.

The effective radiation dose resulting from the administration of 259 MBq (7 mCi) is 4.4 mSv. The radiation doses for this administered dose to the critical organs, which are the kidneys, urinary bladder, and spleen, are 96.2 mGy, 25.4 mGy, and 16.8 mGy, respectively.

These radiation doses are for gallium Ga 68 gozetotide injection alone. If CT or a transmission source are used for attenuation correction, the radiation dose will increase by an amount that varies by technique.

Table 2. Estimated Mean Radiation Absorbed Doses per Activity of Intravenously Administered Gallium Ga 68 Gozetotide Injection in Selected Organs and Tissues
 | Absorbed dose (mGy/MBq)
Organ | Mean | SD
Adrenals | 0.0156 | 0.0014
Brain | 0.0104 | 0.0011
Breasts | 0.0103 | 0.0011
Gallbladder | 0.0157 | 0.0012
Lower colon | 0.0134 | 0.0009
Small intestine | 0.014 | 0.002
Stomach | 0.0129 | 0.0008
Heart | 0.012 | 0.0009
Kidneys | 0.3714 | 0.0922
Liver | 0.0409 | 0.0076
Lungs | 0.0111 | 0.0007
Muscle | 0.0103 | 0.0003
Pancreas | 0.0147 | 0.0009
Red marrow | 0.0114 | 0.0016
Skin | 0.0091 | 0.0003
Spleen | 0.065 | 0.018
Testes | 0.0111 | 0.0006
Thymus | 0.0105 | 0.0006
Thyroid | 0.0104 | 0.0006
Urinary bladder | 0.0982 | 0.0286
Total body | 0.0143 | 0.0013
Effective dose (mSv/MBq) | 0.0169 | 0.0015

3 DOSAGE FORMS AND STRENGTHS

LOCAMETZ is a kit for the preparation of gallium Ga 68 gozetotide injection supplied in a multiple-dose vial containing 25 micrograms of gozetotide as a white lyophilized powder.

Gallium-68 is obtained from one of the following generators:

- Eckert & Ziegler GalliaPharm (Ge 68/Ga 68) generator
- IRE ELiT Galli Eo (Ge 68/Ga 68) generator

After radiolabeling with gallium-68, each vial contains a sterile, clear, colorless solution free from particulate matter of gallium Ga 68 gozetotide at an activity of up to 2,590 MBq (70 mCi) in up to 10 mL at calibration date and time.

4 CONTRAINDICATIONS

None.

5 WARNINGS AND PRECAUTIONS

5.1 Risk for Misinterpretation

Image interpretation errors can occur with LOCAMETZ PET. Negative imaging does not rule out the presence of prostate cancer and positive imaging does not confirm the presence of prostate cancer. Gallium Ga 68 gozetotide uptake is not specific for prostate cancer and may occur with other types of cancer as well as non-malignant processes, such as Paget’s disease, fibrous dysplasia, and osteophytosis. Clinical correlation, which may include histopathological evaluation of the suspected prostate cancer site, is recommended.

The performance of LOCAMETZ for imaging of biochemically recurrent prostate cancer seems to be affected by serum PSA levels and by site of disease. The performance of LOCAMETZ for imaging of metastatic pelvic lymph nodes prior to initial definitive therapy seems to be affected by Gleason score [see Clinical Studies (14.1, 14.2)].

5.2 Radiation Risk

Gallium Ga 68 gozetotide contributes to the patient’s overall long-term cumulative radiation exposure. Long-term cumulative radiation exposure is associated with an increased risk of cancer. Ensure safe handling to minimize radiation exposure to the patient and health care workers. Advise patients to be well hydrated prior to gallium Ga 68 gozetotide injection administration and to void immediately prior to and frequently during the first hours after image acquisition to reduce radiation exposure [see Dosage and Administration (2.1, 2.3)].

6 ADVERSE REACTIONS

6.1 Clinical Trials Experience

Because clinical trials are conducted under widely varying conditions, adverse reaction rates observed in the clinical trials of a drug cannot be directly compared to rates in the clinical trials of another drug and may not reflect the rates observed in practice.

The safety of LOCAMETZ has been established based on three prospective studies of gallium Ga 68 gozetotide in patients with prostate cancer (i.e., Studies 1, 2, and 3). Adverse reactions from these studies are reported below.

In Studies 1 and 2 using another formulation of gallium Ga 68 gozetotide injection, 960 patients received one dose of gallium Ga 68 gozetotide intravenously with the amount (mean ± SD) of radioactivity 188.7 ± 40.7 MBq (5.1 ± 1.1 mCi) [see Clinical Studies (14.1, 14.2)]. The most commonly reported adverse reactions were nausea, diarrhea and dizziness, occurring at a rate of < 1%.

In a randomized, multicenter, open-label clinical study (NCT03511664, referred to as Study 3) in which gallium Ga 68 gozetotide was used to identify PSMA-positive patients on PET imaging to determine eligibility for PSMA-directed therapy, 1,003 patients with progressive metastatic castration-resistant prostate cancer (mCRPC) received one dose of gallium Ga 68 gozetotide intravenously with the amount of radioactivity 167.1 ± 23.1 MBq (4.52 ± 0.62 mCi). Patients were males with median age of 70 years (range, 40 to 94 years), were White (87%), Black or African American (7%), or Asian (2.4%), and had median baseline PSA levels of 74 ng/mL (range, 0 to 8995 ng/mL).

Adverse reactions occurring at ≥ 0.5% in patients with metastatic prostate cancer who received gallium Ga 68 gozetotide injection in Study 3 are presented in Table 3.

Table 3. Adverse Reactions (≥ 0.5%) in Patients with Metastatic Prostate Cancer Who Received Gallium Ga 68 Gozetotide Injection in Study 3
Adverse reactions | Gallium Ga 68 Gozetotide Injection N = 1003 n (%)
General disorders
Fatigue | 12 (1.2)
Gastrointestinal disorders
Nausea | 8 (0.8)
Constipation | 5 (0.5)
Vomiting | 5 (0.5)

Adverse reactions occurring at a rate of < 0.5% in the study were diarrhea, dry mouth, injection site reactions including injection site hematoma and injection site warmth, and chills.

7 DRUG INTERACTIONS

Androgen Deprivation Therapy and Other Therapies Targeting the Androgen Pathway

Androgen deprivation therapy (ADT) and other therapies targeting the androgen pathway, such as androgen receptor antagonists, can result in changes in uptake of gallium Ga 68 gozetotide in prostate cancer. The effect of these therapies on performance of LOCAMETZ PET has not been established.

8 USE IN SPECIFIC POPULATIONS

8.1 Pregnancy

Risk Summary

LOCAMETZ is not indicated for use in females. There are no available data with gallium Ga 68 gozetotide use in pregnant women to evaluate for a drug-associated risk of major birth defects, miscarriage, or adverse maternal or fetal outcomes. All radiopharmaceuticals, including LOCAMETZ, have the potential to cause fetal harm depending on the fetal stage of development and the magnitude of radiation dose. Animal reproduction studies have not been conducted with gallium Ga 68 gozetotide.

8.2 Lactation

Risk Summary

LOCAMETZ is not indicated for use in females. There are no data on the presence of gallium Ga 68 gozetotide in human milk, the effect on the breastfed infant, or the effect on milk production.

8.4 Pediatric Use

The safety and effectiveness of gallium Ga 68 gozetotide in pediatric patients have not been established.

8.5 Geriatric Use

The efficacy of LOCAMETZ in geriatric patients with prostate cancer is based on data from three prospective studies.

Of the total number of patients in Studies 1 and 2 [see Clinical Studies (14.1, 14.2)], 691 of 960 (72%) were 65 years of age and older while 195 (20%) were 75 years of age and older.

Of the total number of patients in Study 3 [see Adverse Reactions (6.1)], 752 of 1,003 (75%) were 65 years of age and older while 284 (28%) were 75 years of age and older.

The efficacy and safety profiles of gallium Ga 68 gozetotide appeared similar in younger adult and geriatric patients with prostate cancer and other reported clinical experience has not identified differences in responses between the elderly and younger patients.

10 OVERDOSAGE

In the event of an overdose of gallium Ga 68 gozetotide, reduce the radiation absorbed dose to the patient where possible by increasing the elimination of the radioactivity from the body by hydration and frequent bladder voiding. A diuretic might also be considered. If possible, an estimate of the effective radiation dose exposure to the patient should be made.

11 DESCRIPTION

11.1 Chemical Characteristics

LOCAMETZ (kit for the preparation of gallium Ga 68 gozetotide injection) is a sterile, radioactive diagnostic agent for intravenous administration after radiolabeling. Each vial contains 25 micrograms of gozetotide, 1 mg gentisic acid, 78 mg of sodium acetate trihydrate, and 40 mg sodium chloride. Gozetotide is also known as PSMA-11.

After reconstitution and radiolabeling of LOCAMETZ, the vial contains gallium Ga 68 gozetotide injection at a radioactivity of up to 2,590 MBq (70 mCi) in up to 10 mL at calibration date and time. The vial also contains hydrochloric acid derived from the gallium-68 chloride solution. Gallium Ga 68 gozetotide injection has a pH between 3.2 to 6.5.

Gallium Ga 68 gozetotide is a urea based peptidomimetic that has a covalently bound chelator (HBED-CC). The peptide has amino acid sequence OH-Glu-CO-Lys(Ahx-CC-HBED)-OH.

Gallium Ga 68 gozetotide has a molecular weight of 1011.91 g/mol. The chemical structure is shown in Figure 3.

Figure 3. Chemical Structure of Gallium Ga 68 Gozetotide

11.2 Physical Characteristics

Gallium-68 decays with a half-life of 68 minutes to stable zinc-68. Table 4 and Table 5 display the principle radiation emission data, and physical decay of gallium-68.

Table 4. Principal Radiation Emission Data (> 1%) for Gallium-68
Radiation/Emission | % Disintegration | Mean energy (MeV)
beta+ | 88% | 0.8360
beta+ | 1.1% | 0.3526
Gamma | 178% | 0.5110
Gamma | 3% | 1.0770
X-ray | 2.8% | 0.0086
X-ray | 1.4% | 0.0086

Table 5. Physical Decay Chart for Gallium-68
Minutes | Fraction remaining
0 | 1
15 | 0.858
30 | 0.736
60 | 0.541
90 | 0.398
120 | 0.293
180 | 0.158
240 | 0.086
360 | 0.025

11.3 Radiation Attenuation

Table 6 displays the radiation attenuation by lead shielding of gallium-68.

Table 6. Radiation Attenuation of 511 keV Photons by Lead (Pb) Shielding
Shield thickness (Pb) mm | Coefficient of attenuation
6 | 0.5
12 | 0.25
17 | 0.1
34 | 0.01
51 | 0.001

12 CLINICAL PHARMACOLOGY

12.1 Mechanism of Action

Gallium Ga 68 gozetotide binds to PSMA. It binds to cells that express PSMA, including malignant prostate cancer cells, which usually overexpress PSMA. Gallium-68 is a β+ emitting radionuclide that allows PET.

12.2 Pharmacodynamics

The relationship between gallium Ga 68 gozetotide plasma concentrations and successful imaging was not explored in clinical trials.

12.3 Pharmacokinetics

Distribution

Intravenously injected gallium Ga 68 gozetotide is cleared from the blood and is accumulated preferentially in the liver (15%), kidneys (7%), spleen (2%), and salivary glands (0.5%). Gallium Ga 68 gozetotide uptake is also seen in the adrenals and prostate. There is no uptake in the cerebral cortex or in the heart, and usually lung uptake is low.

Gozetotide exhibits a mean blood-to-plasma ratio (% CV) of 0.71 (26%) and is approximately 33% bound to human plasma proteins at 1 mcg/mL to 5 mcg/mL in vitro.

Elimination

A total of 14% of the injected dose is excreted in urine in the first 2 hours post-injection.

In Vitro Drug Interaction Studies

CYP450 enzymes

Gozetotide is not a substrate of cytochrome P450 (CYP450) enzymes, not an inhibitor of CYP1A2, CYP2B6, CYP2C8, CYP2C19, CYP2D6 and CYP3A4, and not an inducer of CYP1A2, CYP2B6 and CYP3A4 in vitro.

Transporters

Gozetotide is not a substrate of BCRP, P-gp, MATE1, MATE2-K, OAT1, OAT3 or OCT2. Gozetotide is not an inhibitor of BCRP, P-gp, MATE1, MATE2-K, OAT1, OAT3, OATP1B1, OATP1B3, OCT1 or OCT2 in vitro.

13 NONCLINICAL TOXICOLOGY

13.1 Carcinogenesis, Mutagenesis, Impairment of Fertility

No studies on mutagenic, carcinogenic potential or fertility have been conducted with gallium Ga 68 gozetotide.

14 CLINICAL STUDIES

14.1 Imaging Prior to Initial Definitive Therapy

The efficacy of LOCAMETZ for PET of PSMA-positive lesions in men with prostate cancer with suspected metastasis who are candidates for initial definitive therapy has been established based on a study of another formulation of gallium Ga 68 gozetotide injection. Below is a display of the results of the prospective, open label study PSMA-PreRP (NCT03368547 and NCT02919111, referred to as Study 1).

This two-center study enrolled 325 patients with biopsy-proven prostate cancer who were considered candidates for prostatectomy and pelvic lymph node dissection. All enrolled patients met at least one of the following criteria: serum PSA of at least 10 ng/mL, tumor stage cT2b or greater, or Gleason score greater than 6. Each patient received a single gallium Ga 68 gozetotide PET/CT or PET/MR from mid-thigh to skull base.

A total of 123 patients (38%) proceeded to standard-of-care prostatectomy and template pelvic lymph node dissection and had sufficient histopathology data for evaluation (evaluable patients). Three members of a pool of six central readers independently interpreted each PET scan for the presence of abnormal gallium Ga 68 gozetotide uptake in pelvic lymph nodes located in the common iliac, external iliac, internal iliac, and obturator subregions bilaterally as well as in any other pelvic location. The readers were blinded to all clinical information except for the history of prostate cancer prior to definitive treatment. Extrapelvic sites and the prostate gland itself were not analyzed in this study. For each patient, gallium Ga 68 gozetotide PET results and reference standard histopathology obtained from dissected pelvic lymph nodes were compared by region (left hemipelvis, right hemipelvis, and other).

For the 123 evaluable patients, the mean age was 65 years (range, 45 to 76 years), and 89% were White. The median serum PSA was 11.8 ng/mL. The summed Gleason score was 7 for 44%, 8 for 20%, and 9 for 31% of the patients, with the remainder of the patients having Gleason scores of 6 or 10.

Table 7 compares majority PET reads to pelvic lymph node histopathology results at the patient-level with region matching, such that at least one true positive region defines a true positive patient. As shown, approximately 24% of patients studied were found to have pelvic nodal metastases based on histopathology (95% CI: 17, 32).

Table 7. Patient-Level Performance of Gallium Ga 68 Gozetotide PET for Detection of Pelvic Lymph Node Metastasisa in Men with Prostate Cancer with Suspected Metastasis in Study 1 (n = 123)
 |  | Histopathology |  | Predictive value % (95% CI)
 |  | Positive | Negative
PET scan | Positive | 14 | 9 | PPV 61% (41, 81)
 | Negative | 16 | 84 | NPV 84% (79, 91)
Total |  | 30 | 93
Diagnostic performance % (95% CI) |  | Sensitivity 47% (29, 65) | Specificity 90% (84, 96)
Abbreviations: CI, confidence interval; PPV, positive predictive value; NPV, negative predictive value.
aWith region matching where at least one true positive region defines a true positive patient.

Among the pool of six readers, sensitivity ranged from 36% to 60%, specificity from 83% to 96%, positive predictive value from 38% to 80%, and negative predictive value from 80% to 88%.

In an exploratory subgroup analysis based on summed Gleason score, there was a numerical trend toward more true positives in patients with Gleason score of 8 or higher compared to those with Gleason score of 7 or lower.

An exploratory analysis was performed to estimate the sensitivity and specificity for pelvic nodal metastasis detection in all scanned patients, including the patients who were lacking histopathology reference standard. An imputation method was used based on patient-specific factors. This exploratory analysis resulted in an imputed sensitivity of 47%, with a 95% confidence interval (CI) ranging from 38% to 55%, and an imputed specificity of 74%, with a 95% CI ranging from 68% to 80% for all patients imaged with gallium Ga 68 gozetotide PET.

14.2 Imaging Prior to Suspected Recurrence Therapy

The efficacy of LOCAMETZ for PET of PSMA-positive lesions in men with prostate cancer with suspected recurrence based on elevated serum PSA level has been established based on studies of another formulation of gallium Ga 68 gozetotide injection. Below is a display of the result of the prospective, open label study PSMA-BCR (NCT02940262 and NCT02918357, referred to as Study 2).

This two-center study enrolled 635 patients with biochemical evidence of recurrent prostate cancer after definitive therapy, defined by serum PSA of > 0.2 ng/mL more than 6 weeks after prostatectomy or by an increase in serum PSA of at least 2 ng/mL above nadir after definitive radiotherapy. All patients received a single gallium Ga 68 gozetotide PET/CT or PET/MR from mid-thigh to skull base. Three members of a pool of nine independent central readers evaluated each scan for the presence and regional location (20 subregions grouped into four regions) of abnormal gallium Ga 68 gozetotide uptake suggestive of recurrent prostate cancer. The readers were blinded to all clinical information other than type of primary therapy and most recent serum PSA level.

A total of 469 patients (74%) had at least one positive region detected by gallium Ga 68 gozetotide PET majority read. The distribution of gallium Ga 68 gozetotide PET positive regions was 34% bone, 25% prostate bed, 25% pelvic lymph node, and 17% extrapelvic soft tissue. Two hundred and ten patients had composite reference standard information collected in a PET positive region (evaluable patients), consisting of at least one of the following: histopathology, imaging (bone scintigraphy, CT, or MRI) acquired at baseline or within 12 months after gallium Ga 68 gozetotide PET, or serial serum PSA. Composite reference standard information for gallium Ga 68 gozetotide PET negative regions was not systematically collected in this study.

In the 210 evaluable patients, the mean age was 70 years (range, 49 to 88 years) and 82% were 65 years of age or older. White patients made up 90% of the group. The median serum PSA was 3.6 ng/mL. Prior treatment included radical prostatectomy in 64% and radiotherapy in 73%.

Of the 210 evaluable patients, 192 patients (91%) were found to be true positive in one or more regions against the composite reference standard (95% CI: 88%, 95%). Among the pool of nine readers used in the study, the proportion of patients who were true positive in one or more regions ranged from 82% to 97%. The prostate bed had the lowest proportion of true positive results at the region-level (76% versus 96% for non-prostate regions).

An exploratory analysis was also performed in which gallium Ga 68 gozetotide PET positive patients who lacked reference standard information were imputed using an estimated likelihood that at least one location-matched PET positive lesion was reference standard positive based on patient-specific factors. In this exploratory analysis, 340 of 475 patients (72%) were imputed as true positive in one or more regions (95% CI: 68%, 76%).

In another exploratory analysis using the same imputation approach for PET positive patients who lacked reference standard information, 340 of 635 patients (54%) were correctly detected as true positive (95% CI: 50%, 57%) among all BCR patients who received a PET scan, whether it was read as positive or negative. The likelihood of identifying a gallium Ga 68 gozetotide PET positive lesion in this study generally increased with higher serum PSA level. Table 8 shows the patient-level gallium Ga 68 gozetotide PET results stratified by serum PSA level. The mean time between PSA measurement and PET scan was 40 days with a range of 0 to 367 days. Percent PET positivity was calculated as the proportion of patients with a positive gallium Ga 68 gozetotide PET out of all patients scanned. Percent PET positivity includes patients determined to be either true positive or false positive as well as those in whom such determination was not made due to the absence of composite reference standard data.

Table 8. Patient-Level Gallium Ga 68 Gozetotide PET Results and Percent PET Positivity Stratified by Serum PSA Level in Men with Prostate Cancer with Suspected Recurrence in Study 2 (n = 628)a
 | PET-positive patients
PSA (ng/mL) | Total | TP | FP | Without reference standard | PET-negative patients | PET positivity %b (95% CI)
 |  | With reference standard
< 0.5 | 48 | 11 | 1 | 36 | 87 | 36% (27, 44)
 |  | 12
≥ 0.5 and < 1 | 44 | 15 | 3 | 26 | 35 | 56% (45, 67)
 |  | 18
≥ 1 and < 2 | 71 | 29 | 1 | 41 | 15 | 83% (75, 91)
 |  | 30
≥ 2 | 299 | 137 | 13 | 149 | 29 | 91% (88, 94)
 |  | 150
Total | 462 | 192 | 18 | 252 | 166 | 74% (70, 77)
 |  | 210
Abbreviations: PET, positron emission tomography; PSA, prostate-specific antigen; PSMA, prostate-specific membrane antigen; BCR, biochemical recurrence; TP, true positive; FP, false positive.
a7 patients were excluded from this table due to protocol deviations.
bPercent PET positivity: PET positive patients/total patients scanned.

14.3 Imaging to Select Patients for PSMA-Directed Therapy

Refer to the prescribing information of the PSMA-directed therapy for description of the studies in which the efficacy of LOCAMETZ for selecting patients has been established.

16 HOW SUPPLIED/STORAGE AND HANDLING

How Supplied

LOCAMETZ is supplied as a kit for the preparation of gallium Ga 68 gozetotide injection in a carton of 1 vial (NDC# 0078-1224-61).

Each multiple-dose vial contains 25 micrograms of gozetotide as white lyophilized powder packaged in a 10 mL type I Plus glass vial closed with a rubber stopper and sealed with a flip-off cap.

Storage and Handling

Before radiolabeling, store at 2°C to 25°C (36°F to 77°F). Do not freeze.

After radiolabeling, store upright with an appropriate lead shielding to protect from radiation, below 30°C (86°F). Do not freeze. After radiolabeling, use within 6 hours.

This preparation is approved for use by persons under license by the Nuclear Regulatory Commission or the relevant regulatory authority of an Agreement State.

17 PATIENT COUNSELING INFORMATION

Adequate Hydration

Advise patients to be well hydrated prior to the administration of gallium Ga 68 gozetotide injection and urge them to urinate immediately prior to image acquisition and frequently during the first hours following administration to reduce radiation exposure [see Dosage and Administration (2.3), Warnings and Precautions (5.2)].

Distributed by:
Novartis Pharmaceuticals Corporation
East Hanover, NJ 07936

©2025 Novartis

LOCAMETZ® is a registered trademark of Novartis AG and/or its affiliates.

U.S. Patent 11369590

T2025-37

PRINCIPAL DISPLAY PANEL

LOCAMETZ®

kit for the preparation of
gallium Ga 68 gozetotide injection
25 mcg per vial gozetotide

For Intravenous Use Only

Radiolabel with gallium-68 chloride
before use

Rx Only

NDC 0078-1224-61

Novartis Pharmaceuticals Corporation
East Hanover, NJ 07936